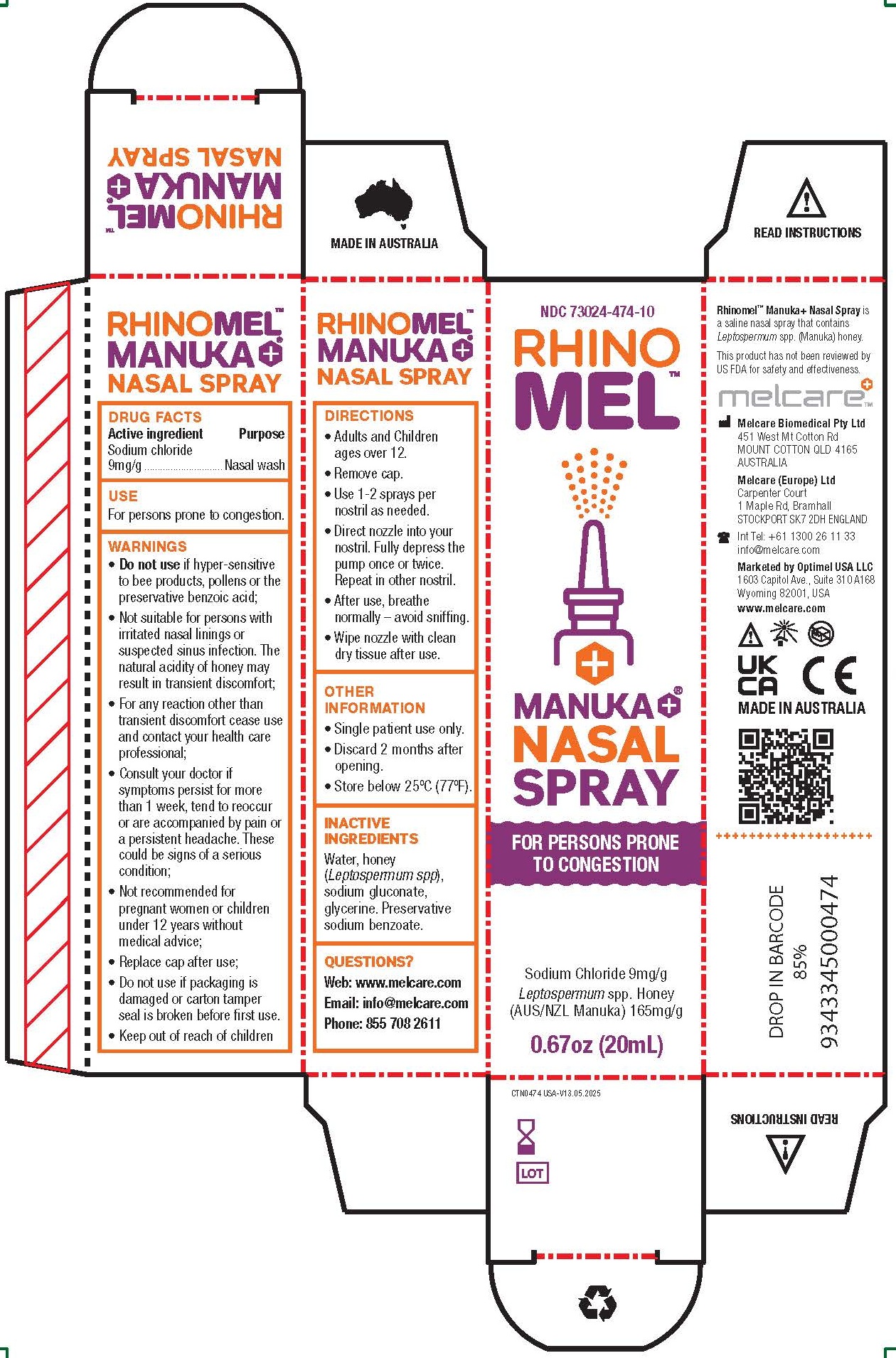 DRUG LABEL: Rhinomel Manuka
NDC: 73024-474 | Form: SPRAY
Manufacturer: Melcare Biomedical Pty Ltd
Category: otc | Type: HUMAN OTC DRUG LABEL
Date: 20251209

ACTIVE INGREDIENTS: SODIUM CHLORIDE 9 mg/1 mL
INACTIVE INGREDIENTS: SODIUM BENZOATE; HONEY; WATER; SODIUM GLUCONATE; GLYCERIN

Rhinomel Manuka+ Nasal Spray

Drug Facts

Active ingredients

Sodium chloride

Purpose

Nasal Wash

Uses

For persons prone to congestion

Warnings

• Do not use if hyper-sensitive

to bee products, pollens or the

preservative benzoic acid;

• Not suitable for persons with

irritated nasal linings or

suspected sinus infection. The

natural acidity of honey may

result in transient discomfort;

• For any reaction other than

transient discomfort cease use

and contact your health care

professional;

• Consult your doctor if

symptoms persist for more

than 1 week, tend to reoccur

or are accompanied by pain or

a persistent headache. These

could be signs of a serious

condition;

• Not recommended for

pregnant women or children

under 12 years without

medical advice;

• Replace cap after use;

• Do not use if packaging is

damaged or carton tamper

seal is broken before first use.

• Keep out of reach of children

Directions

• Adults and Children

ages over 12.

• Remove cap.

• Use 1-2 sprays per

nostril as needed.

• Direct nozzle into your

nostril. Fully depress the

pump once or twice.

Repeat in other nostril.

• After use, breathe

normally – avoid sniffing.

• Wipe nozzle with clean

dry tissue after use.

Other Information

- Single patient use only.
- Discard 2 months after opening.
- Store below 25°C (77°F)

Inactive Ingredients

Water, honey (Leptospermum spp), sodium gluconate, glycerine. Preservative sodium benzoate.

Questions?

Web: www.melcare.com
Email: info@melcare.com
Phone: 855 708 2611